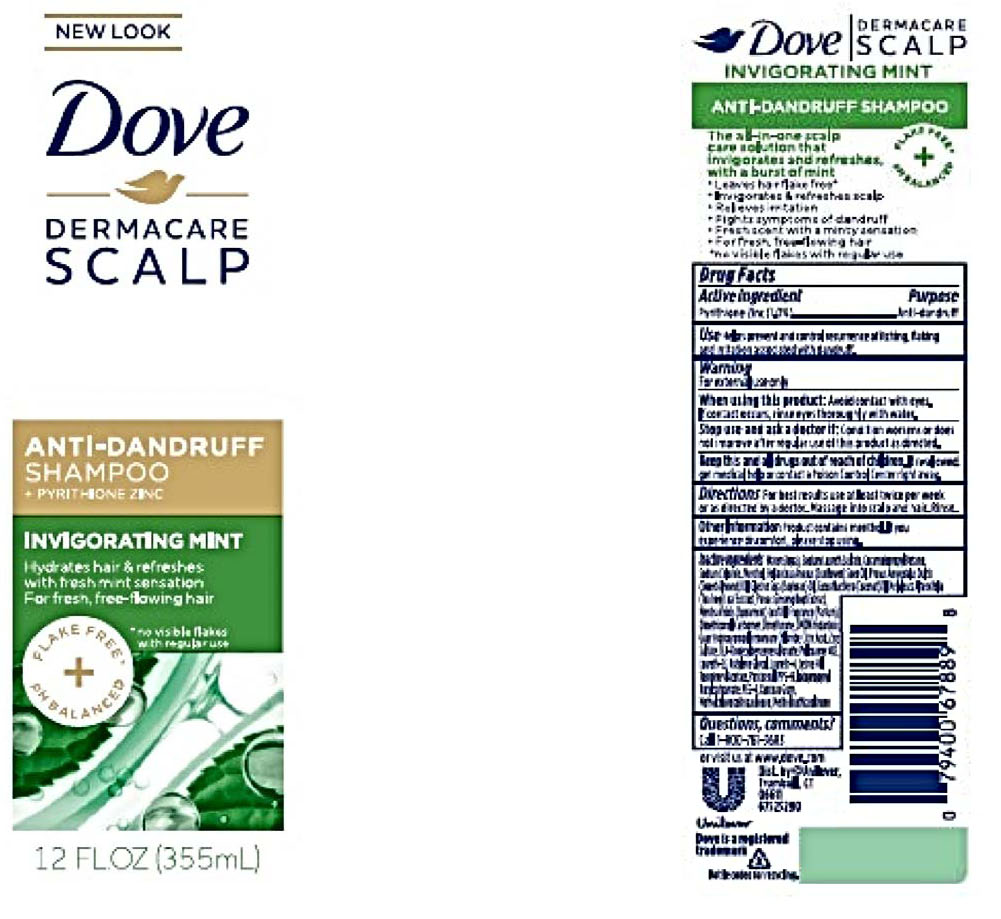 DRUG LABEL: Dove
NDC: 64942-1625 | Form: SHAMPOO
Manufacturer: Conopco, Inc. d/b/a/ Unilever
Category: otc | Type: HUMAN OTC DRUG LABEL
Date: 20221207

ACTIVE INGREDIENTS: PYRITHIONE ZINC 1 g/100 mL
INACTIVE INGREDIENTS: WATER; SODIUM LAURETH-3 SULFATE; COCAMIDOPROPYL BETAINE; SODIUM CHLORIDE; MENTHOL, UNSPECIFIED FORM; SUNFLOWER OIL; ALMOND OIL; SOYBEAN OIL; COCONUT OIL; TEA TREE OIL; ASIAN GINSENG; SPEARMINT OIL; DIMETHICONOL (40 CST); CARBOMER HOMOPOLYMER TYPE C (ALLYL PENTAERYTHRITOL CROSSLINKED); DIMETHICONE; DMDM HYDANTOIN; GUAR HYDROXYPROPYLTRIMONIUM CHLORIDE (1.7 SUBSTITUENTS PER SACCHARIDE); CITRIC ACID MONOHYDRATE; ZINC SULFATE, UNSPECIFIED FORM; TRIETHANOLAMINE DODECYLBENZENESULFONATE; POLOXAMER 407; LAURETH-23; BUTYLENE GLYCOL; LAURETH-4; LYSINE HYDROCHLORIDE; .ALPHA.-TOCOPHEROL ACETATE, D-; PANTHENOL; PPG-9; IODOPROPYNYL BUTYLCARBAMATE; POLYETHYLENE GLYCOL 200; XANTHAN GUM; METHYLCHLOROISOTHIAZOLINONE; METHYLISOTHIAZOLINONE

Dove Dermacare Scalp Invigorating Mint Anti-Dandruff Shampoo

DOVE DERMACARE SCALP INVIGORATING MINT ANTI-DANDRUFF SHAMPOO - pyrithione zinc shampoo

Dove Dermacare Scalp Invigorating Mint Anti-Dandruff Shampoo

Drug Facts

Active ingredient
Pyrithione Zinc (1.0%)

Purpose

Anti-dandruff

Use

Helps prevent and control recurrence of itching, flaking and irritation associated with dandruff.

Warnings

For external use only
When using this product Avoid contact with eyes. If contact occurs, rinse eyes thoroughly with water.
Stop use and ask a doctor if Condition worsens or does not improve after regular use of this product as directed.

KEEP OUT OF REACH OF CHILDREN

Keep this and all drugs out of reach of children. If swallowed, get medical help or contact a Poison Control Center right away.

Directions

For best results use at least twice per week or as directed by a doctor. Massage into scalp and hair. Rinse.

Other Information

Product contains menthol. If you experience discomfort, please stop using.

Inactive Ingredients

Water (Aqua), Sodium Laureth Sulfate, Cocamidopropyl Betaine, Sodium Chloride, Menthol, Helianthus Annuus (Sunflower) Seed Oil, Prunus Amygdalus Dulcis (Sweet Almond) Oil, Glycine Soja (Soybean) Oil, Cocos Nucifera (Coconut) Oil, Melaleuca Alternifolia (Tea Tree) Leaf Extract, Panax Ginseng Root Extract, Mentha Viridis (Spearmint) Leaf Oil, Fragrance (Parfum), Dimethiconol, Carbomer, Dimethicone, DMDM Hydantoin, Guar Hydroxypropyltrimonium Chloride, Citric Acid, Zinc Sulfate, TEA-Dodecylbenzenesulfonate, Poloxamer 407, Laureth-23, Butylene Glycol, Laureth-4, Lysine HCl, Tocopheryl Acetate, Panthenol, PPG-9, Iodopropynyl Butylcarbamate, PEG-4, Xanthan gum, Methylchloroisothiazolinone, Methylisothiazolinone.

Questions, comments?

Call 1-800-761-3683